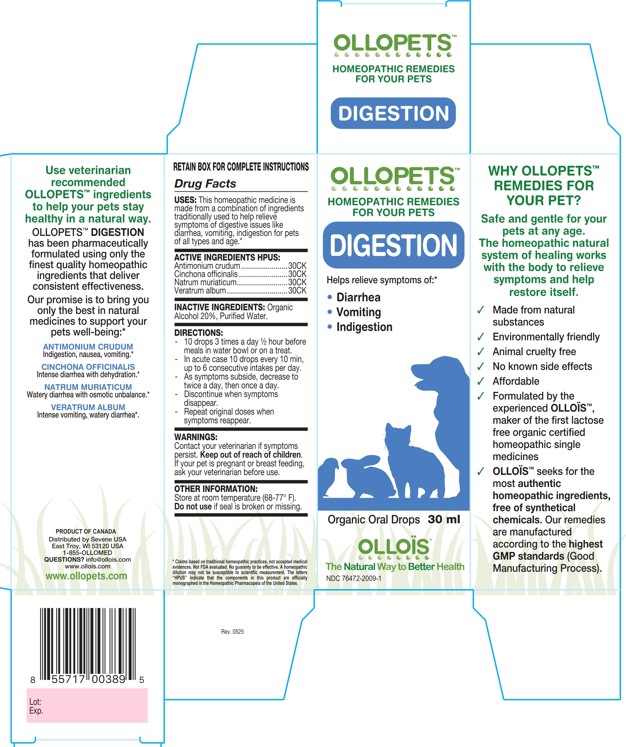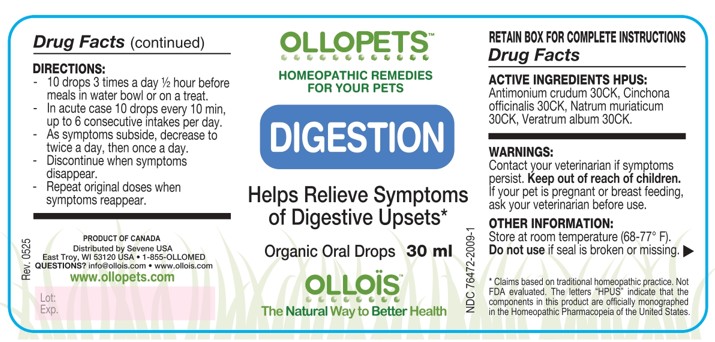 DRUG LABEL: OLLOPETS DIGESTION
NDC: 76472-2009 | Form: SOLUTION
Manufacturer: SEVENE USA
Category: homeopathic | Type: OTC ANIMAL DRUG LABEL
Date: 20260218

ACTIVE INGREDIENTS: ANTIMONY TRISULFIDE 30 [hp_C]/100 mL; CINCHONA OFFICINALIS BARK 30 [hp_C]/100 mL; SODIUM CHLORIDE 30 [hp_C]/100 mL; VERATRUM ALBUM ROOT 30 [hp_C]/100 mL
INACTIVE INGREDIENTS: ALCOHOL; WATER

SEVENE USA - OLLOPETS - DIGESTION

ACTIVE INGREDIENT HPUS

Antimonium crudum.......................30CK
Cinchona officinalis ........................30CK
Natrum muriaticum.........................30CK
Veratrum album..............................30CK